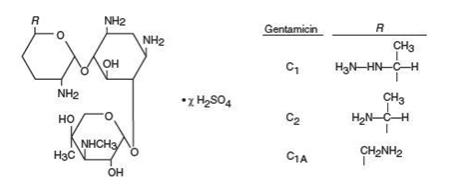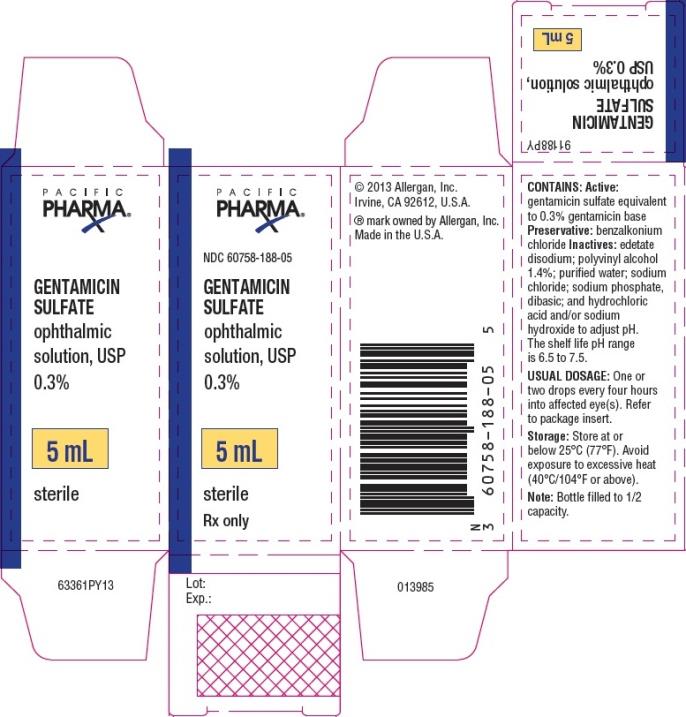 DRUG LABEL: GENTAMICIN SULFATE
NDC: 67296-0370 | Form: SOLUTION/ DROPS
Manufacturer: Redpharm Drug
Category: prescription | Type: HUMAN PRESCRIPTION DRUG LABEL
Date: 20240626

ACTIVE INGREDIENTS: GENTAMICIN SULFATE 3 mg/1 mL
INACTIVE INGREDIENTS: EDETATE DISODIUM; POLYVINYL ALCOHOL, UNSPECIFIED; WATER; SODIUM CHLORIDE; SODIUM PHOSPHATE, DIBASIC; BENZALKONIUM CHLORIDE; HYDROCHLORIC ACID; SODIUM HYDROXIDE

GENTAMICIN SULFATE
ophthalmicsolution, USP 0.3%
sterile

DESCRIPTION

Gentamicin sulfate ophthalmic solution, USP is a sterile, topical anti-infective agent for ophthalmic use.

Gentamicin is obtained from cultures of Micromonospora purpurea. It is a mixture of the sulfate salts of gentamicin C1, C2, and C1A. All three components appear to have similar antimicrobial activity. Gentamicin sulfate occurs as a white to buff powder and is soluble in water and insoluble in alcohol. The structural formula is as follows:

Each mL contains: Active:gentamicin sulfate equivalent to 3 mg (0.3%) gentamicin base. Preservative:benzalkonium chloride. Inactives:edetate disodium; polyvinyl alcohol 1.4%; purified water; sodium chloride; sodium phosphate, dibasic; and hydrochloric acid and/or sodium hydroxide may be added to adjust pH. The solution is an aqueous, buffered solution with a shelf life pH range of 6.5 to 7.5.

CLINICAL PHARMACOLOGY

Microbiology

Gentamicin sulfate is active in vitroagainst many strains of the following microorganisms: Staphylococcus aureus, Staphylococcus epidermidis, Streptococcus pyogenes, Streptococcus pneumoniae, Enterobacter aerogenes, Escherichia coli, Haemophilus influenzae, Klebsiella pneumoniae, Neisseria gonorrhoeae, Pseudomonas aeruginosa,and Serratia marcescens.

INDICATIONS AND USAGE

Gentamicin sulfate ophthalmic solution, USP is indicated in the topical treatment of ocular bacterial infections including conjunctivitis, keratitis, keratoconjunctivitis, corneal ulcers, blepharitis, blepharoconjunctivitis, acute meibomianitis, and dacryocystitis, caused by susceptible strains of the following microorganisms: Staphylococcus aureus, Staphylococcus epidermidis, Streptococcus pyogenes, Streptococcus pneumoniae, Enterobacter aerogenes, Escherichia coli, Haemophilus influenzae, Klebsiella pneumoniae, Neisseria gonorrhoeae, Pseudomonas aeruginosa,and Serratia marcescens.

CONTRAINDICATIONS

Gentamicin sulfate ophthalmic solution, USP is contraindicated in patients with known hypersensitivity to any of its components.

WARNINGS

NOT FOR INJECTION INTO THE EYE.

Gentamicin sulfate ophthalmic solution, USP is not for injection. It should never be injected subconjunctivally, nor should it be directly introduced into the anterior chamber of the eye.

PRECAUTIONS

General

Prolonged use of topical antibiotics may give rise to overgrowth of nonsusceptible microorganisms, including fungi. Bacterial resistance to gentamicin may also develop. If purulent discharge, inflammation or pain becomes aggravated, the patient should discontinue use of the medication and consult a physician.

If irritation or hypersensitivity to any component of the drug develops, the patient should discontinue use of this preparation and appropriate therapy should be instituted.

Information for Patients

To avoid contamination, do not touch tip of container to the eye, eyelid or any surface.

Carcinogenesis, Mutagenesis, Impairment of Fertility

There are no published carcinogenicity or impairment of fertility studies on gentamicin. Aminoglycoside antibiotics have been found to be non-mutagenic.

Pregnancy

Gentamicin has been shown to depress body weights, kidney weights and median glomerular counts in newborn rats when administered systemically to pregnant rats in daily doses approximately 500 times the maximum recommended ophthalmic human dose. There are no adequate and well-controlled studies in pregnant women. Gentamicin should be used during pregnancy only if the potential benefit justifies the potential risk to the fetus.

Pediatric Use

Safety and effectiveness in neonates have not been established.

ADVERSE REACTIONS

Bacterial and fungal corneal ulcers have developed during treatment with gentamicin ophthalmic preparations.

The most frequently reported adverse reactions are ocular burning and irritation upon drug instillation, non-specific conjunctivitis, conjunctival epithelial defects and conjunctival hyperemia.

Other adverse reactions which have occurred rarely are allergic reactions, thrombocytopenic purpura and hallucinations.

DOSAGE AND ADMINISTRATION

Instill one or two drops into the affected eye(s) every four hours. In severe infections, dosage may be increased to as much as two drops every hour.

HOW SUPPLIED

Gentamicin sulfate ophthalmic solution, USP 0.3% is supplied sterile in white opaque LDPE plastic bottles and tips with beige high impact polystyrene (HIPS) caps as follows:

5 mL in 10 mL bottle – NDC 60758-188-05

Storage:

Store at or below 25°C (77°F). Avoid exposure to excessive heat (40°C/104°F or above).

Revised: 10/2017

Distributed for: Allergan USA, Inc.
Madison, NJ 07940

©2017 Allergan. All rights reserved.
All trademarks are the property of their respective owners.
Made in the U.S.A.

v1.0USPI188

PRINCIPAL DISPLAY PANEL

NDC 60758-188-05
GENTAMICIN
SULFATE
ophthalmic
solution, USP
0.3%
5 mL
sterile
Rx Only